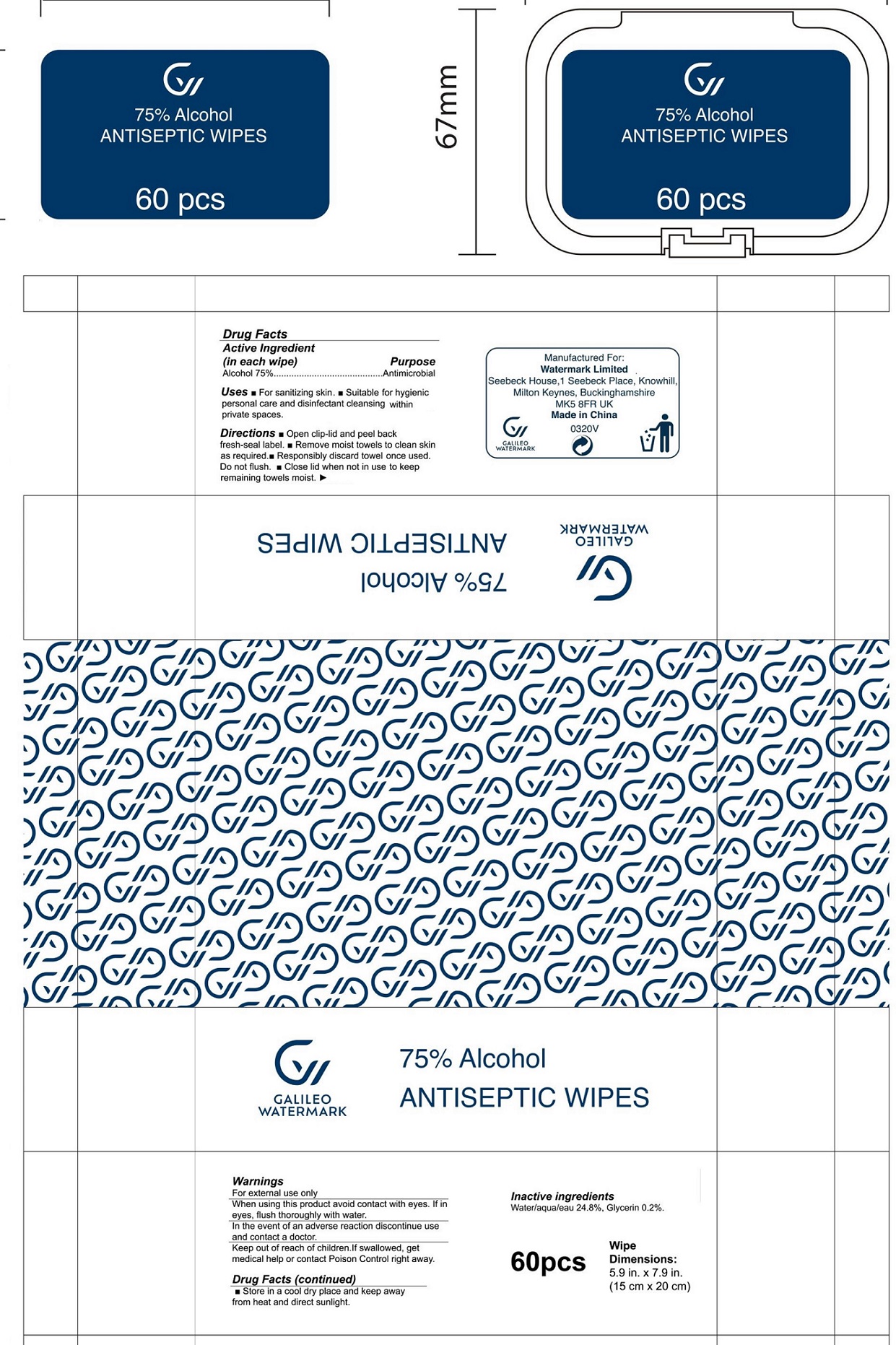 DRUG LABEL: 75 Alcohol Antiseptic Wipes
NDC: 78405-001 | Form: CLOTH
Manufacturer: WATERMARK LIMITED
Category: otc | Type: HUMAN OTC DRUG LABEL
Date: 20231213

ACTIVE INGREDIENTS: ALCOHOL 0.75 mL/1 mL
INACTIVE INGREDIENTS: WATER; GLYCERIN

75% Alcohol Antiseptic Wipes

Active Ingredient (in each wipe)

Alcohol 75%

Purpose

Antimicrobial

Uses

- For sanitizing skin.
- Suitable for hygienic personal care and disinfectant cleansing within private spaces.

Directions

- Open clip-lid and peel back fresh-seal label.
- Remove moist towels to clean skin as required.
- Responsibly discard towel once used. Do not flush.
- Close lid when not in use to keep remaining towels moist.

Warnings

For external use only

When using this product

avoid contact with eyes. If in eyes, flush thoroughly with water. In the event of an adverse reaction discontinue use and contact a doctor.

Keep out of reach of children.

If swallowed, get medical help or contact Poison Control right away.

Store in a cool dry place and keep away from heat and direct sunlight.

Inactive ingredients

Water/aqua 24.8%, Glycerin 0.2%.